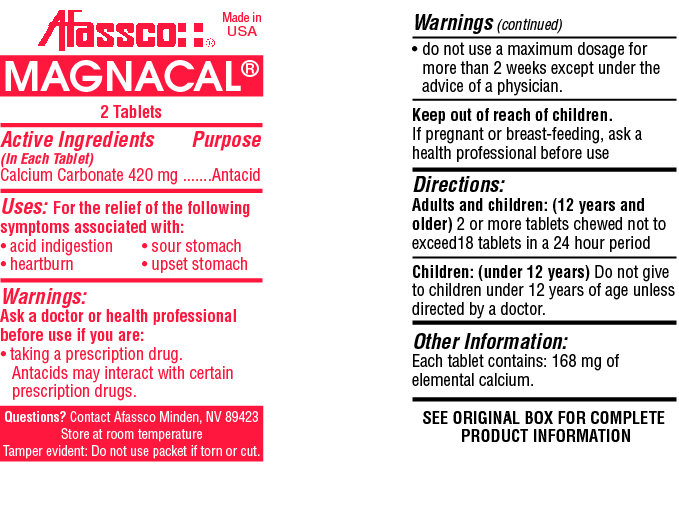 DRUG LABEL: Magnacal
NDC: 51532-0303 | Form: TABLET, CHEWABLE
Manufacturer: Afassco Inc.
Category: otc | Type: HUMAN OTC DRUG LABEL
Date: 20190921

ACTIVE INGREDIENTS: CALCIUM CARBONATE 420 1/1 1
INACTIVE INGREDIENTS: STARCH, CORN; SUCROSE; MAGNESIUM STEARATE; MINT; ACACIA; MALTODEXTRIN

ACTIVE INGREDIENT IN EACH TABLET- CALCIUM CARBONATE 420 MG

PURPOSE

ANTACID

INDICATIONS AND USAGE

Uses: For the relief of the following symptoms associated with:

• acid indigestion • sour stomach

• heartburn • upset stomach

Warnings:

Ask a doctor or health professional before use if you are:

• taking a prescription drug. Antacids may interact with certain prescription drugs.

• do not use a maximum dosage for more than 2 weeks except under the advice of a physician.

PREGNANCY OR BREAST FEEDING

If pregnant or breast-feeding baby, ask a health professional before use.

KEEP OUT OF REACH OF CHILDREN.

In case of overdose, get medical help or contact a Poison Control Center right away. Prompt medical attention is critical for adults as well as for children even if you do not notice any signs or symptoms.

Directions:

Adults and children: (12 years and older) 2 or more tablets chewed not to exceed18 tablets in a 24 hour period

Children: (under 12 years) Do not give to children under 12 years of age unless directed by a doctor.

INACTIVE INGREDIENT

SEE ORIGINAL BOX FOR COMPLETE PRODUCT INFORMATION

Other Information:

Each tablet contains: 168 mg of elemental calcium.

PACKAGE LABEL

res